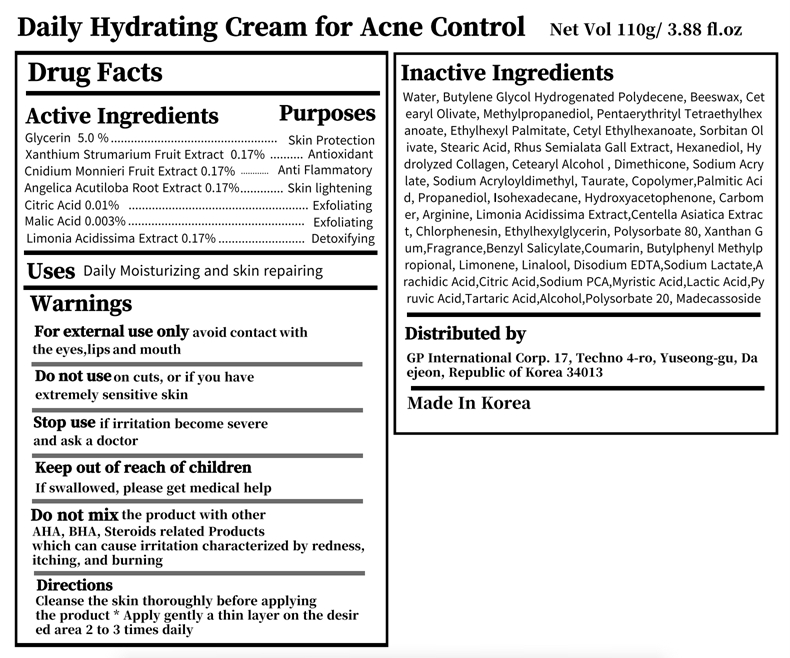 DRUG LABEL: Refresh Nature Cream
NDC: 82790-301 | Form: CREAM
Manufacturer: GP International Corp.
Category: otc | Type: HUMAN OTC DRUG LABEL
Date: 20220622

ACTIVE INGREDIENTS: XANTHIUM STRUMARIUM FRUIT 0.17 g/100 g; CNIDIUM MONNIERI FRUIT 0.17 g/100 g; MALIC ACID 0.003 g/100 g; GLYCERIN 5 g/100 g; ANGELICA ACUTILOBA ROOT 0.17 g/100 g; LIMONIA ACIDISSIMA WHOLE 0.17 g/100 g; CITRIC ACID MONOHYDRATE 0.01 g/100 g
INACTIVE INGREDIENTS: STEARIC ACID; SODIUM ACRYLOYLDIMETHYLTAURATE; TAURINE; GLATIRAMER ACETATE; POLYSORBATE 20; MADECASSOSIDE; MARINE COLLAGEN, SOLUBLE; SODIUM ACRYLATE; BUTYLENE GLYCOL; HYDROGENATED POLYDECENE TYPE I; LACTIC ACID; ISOHEXADECANE; HYDROXYACETOPHENONE; ARACHIDIC ACID; SODIUM PYRROLIDONE CARBOXYLATE; MYRISTIC ACID; PALMITIC ACID; YELLOW WAX; CETEARYL OLIVATE; METHYLPROPANEDIOL; PENTAERYTHRITYL TETRAETHYLHEXANOATE; CARBOMER HOMOPOLYMER, UNSPECIFIED TYPE; XANTHAN GUM; BUTYLPHENYL METHYLPROPIONAL; RHUS CHINENSIS GALL; CETOSTEARYL ALCOHOL; ETHYLHEXYLGLYCERIN; BENZYL SALICYLATE; COUMARIN; LIMONENE, (+/-)-; PROPANEDIOL; ARGININE; CENTELLA ASIATICA TRITERPENOIDS; POLYSORBATE 80; LINALOOL, (+/-)-; SORBITAN OLIVATE; HEXANEDIOL; DIMETHICONE; WATER; ETHYLHEXYL PALMITATE; CETYL ETHYLHEXANOATE; FRAGRANCE LEMON ORC2001060; CHLORPHENESIN; EDETATE DISODIUM ANHYDROUS; SODIUM LACTATE; PYRUVIC ACID; TARTARIC ACID; ALCOHOL

82790

purpose

Acne Control

Use

Daily Moisturizing and skin repairing

Warnings

Do not use on cuts, or if you have extremely sensitive skin

Do not mix the product with other AHA, BHA, Steroids related Products

which can cause irritation characterized by redness,

itching, and burning

Warnings

When using this product do not use in or near the eyes.

Warnings

Stop use if irritation become severe and ask a doctor

Warnings

For external use only avoid contact with the eyes,lips and mouth

Warnings

Keep out of reach of children If swallowed, please get medical help

Directions

Directions Cleanse the skin thoroughly before applying

the product * Apply gently a thin layer on the desired area 2 to 3 times daily

active ingredient

Glycerin 5.0 % Skin Protection

Xanthium Strumarium Fruit Extract 0.17% Antioxidant

Cnidium Monnieri Fruit Extract 0.17% Anti Flammatory

Angelica Acutiloba Root Extract 0.17% Skin lightening

Citric Acid 0.01% Exfoliating

Malic Acid 0.003% Exfoliating

Inactive Ingredients

Water, Butylene Glycol Hydrogenated Polydecene, Beeswax, Cetearyl Olivate, Methylpropanediol, Pentaerythrityl Tetraethylhexanoate, Ethylhexyl Palmitate, Cetyl Ethylhexanoate, Sorbitan Olivate, Stearic Acid, Rhus Semialata Gall Extract, Hexanediol, Hydrolyzed Collagen, Cetearyl Alcohol , Dimethicone, Sodium Acrylate, Sodium Acryloyldimethyl, Taurate, Copolymer,Palmitic Acid, Propanediol, Isohexadecane, Hydroxyacetophenone, Carbomer, Arginine, Limonia Acidissima Extract,Centella Asiatica Extract, Chlorphenesin, Ethylhexylglycerin, Polysorbate 80, Xanthan Gum,Fragrance,Benzyl Salicylate,Coumarin, Butylphenyl Methylpropional, Limonene, Linalool, Disodium EDTA,Sodium Lactate,Arachidic Acid,Citric Acid,Sodium PCA,Myristic Acid,Lactic Acid,Pyruvic Acid,Tartaric Acid,Alcohol,Polysorbate 20, Madecassoside

Daily Hydrating Cream for Acne Control